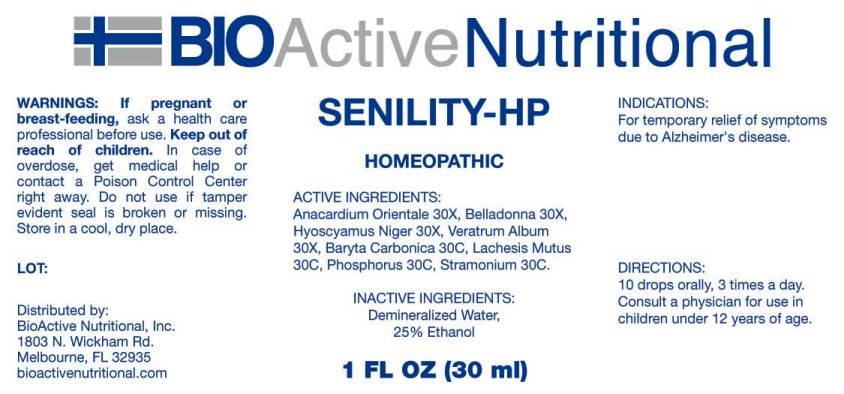 DRUG LABEL: Senility HP
NDC: 43857-0254 | Form: LIQUID
Manufacturer: BioActive Nutritional, Inc.
Category: homeopathic | Type: HUMAN OTC DRUG LABEL
Date: 20170223

ACTIVE INGREDIENTS: SEMECARPUS ANACARDIUM JUICE 30 [hp_X]/1 mL; ATROPA BELLADONNA 30 [hp_X]/1 mL; HYOSCYAMUS NIGER 30 [hp_X]/1 mL; VERATRUM ALBUM ROOT 30 [hp_X]/1 mL; BARIUM CARBONATE 30 [hp_C]/1 mL; LACHESIS MUTA VENOM 30 [hp_C]/1 mL; PHOSPHORUS 30 [hp_C]/1 mL; DATURA STRAMONIUM 30 [hp_C]/1 mL
INACTIVE INGREDIENTS: WATER; ALCOHOL

Drug Facts:

ACTIVE INGREDIENTS:

Anacardium Orientale 30X, Belladonna 30X, Hyoscyamus Niger 30X, Veratrum Album 30X, Baryta Carbonica 30C, Lachesis Mutus 30C, Phosphorus 30C, Stramonium 30C.

INDICATIONS:

For temporary relief of symptoms due to Alzheimer's disease.

WARNINGS:

If pregnant or breast-feeding, ask a health care professional before use.

Keep out of reach of children. In case of overdose, get medical help or contact a Poison Control Center right away.

Do not use if tamper evident seal is broken or missing.

Store in a cool, dry place.

Keep out of reach of children. In case of overdose, get medical help or contact a Poison Control Center right away.

DIRECTIONS:

10 drops orally, 3 times a day. Consult a physician for use in children under 12 years of age.

INDICATIONS:

For temporary relief of symptoms due to Alzheimer's disease.

INACTIVE INGREDIENTS:

Demineralized Water, Ethanol 25%

QUESTIONS:

Distributed by:
BioActive Nutritional, Inc.
1803 N. Wickham Rd.
Melbourne, FL 32935
bioactivenutritional.com

PACKAGE LABEL DISPLAY:

BIOActive Nutritional

SENILITY HP

HOMEOPATHIC

1 FL OZ (30 ml)